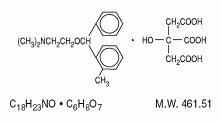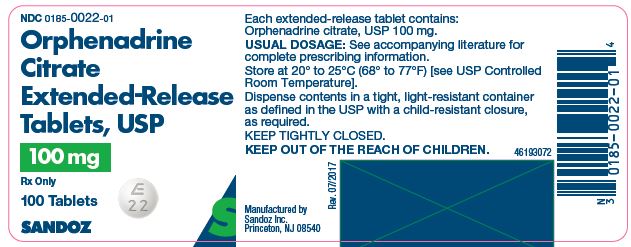 DRUG LABEL: Orphenadrine Citrate
NDC: 67296-1077 | Form: TABLET, EXTENDED RELEASE
Manufacturer: RedPharm Drug
Category: prescription | Type: HUMAN PRESCRIPTION DRUG LABEL
Date: 20240711

ACTIVE INGREDIENTS: ORPHENADRINE CITRATE 100 mg/1 1
INACTIVE INGREDIENTS: CALCIUM STEARATE; ETHYLCELLULOSE, UNSPECIFIED; LACTOSE MONOHYDRATE

Orphenadrine Citrate Extended-Release Tablets, USP

Rx Only

DESCRIPTION

Orphenadrine citrate, USP is the citrate salt of orphenadrine (2-dimethyl-aminoethyl 2-methylbenzhydryl ether citrate). It occurs as a white, crystalline powder having a bitter taste. It is practically odorless; sparingly soluble in water, slightly soluble in alcohol and has a molecular weight of 461.51. The molecular formula C18H23NO • C6H8O7is represented by the following structural formula:

Each orphenadrine citrate extended-release tablet, USP contains 100 mg orphenadrine citrate, USP. Orphenadrine citrate extended-release tablets, USP also contain: calcium stearate, ethylcellulose and lactose monohydrate.

CLINICAL PHARMACOLOGY

The mode of therapeutic action has not been clearly identified, but may be related to its analgesic properties. Orphenadrine citrate does not directly relax tense skeletal muscles in man. Orphenadrine citrate also possesses anti-cholinergic actions.

INDICATIONS AND USAGE

Orphenadrine citrate extended-release tablets are indicated as an adjunct to rest, physical therapy and other measures for the relief of discomfort associated with acute painful musculo skeletal conditions.

CONTRAINDICATIONS

Contraindicated in patients with glaucoma, pyloric or duodenal obstruction, stenosing peptic ulcers, prostatic hypertrophy or obstruction of the bladder neck, cardio-spasm (megaesophagus) and myasthenia gravis.

Contraindicated in patients who have demonstrated a previous hypersensitivity to the drug.

WARNINGS

Some patients may experience transient episodes of light-headedness, dizziness or syncope. Orphenadrine citrate may impair the ability of the patient to engage in potentially hazardous activities such as operating machinery or driving a motor vehicle; ambulatory patients should therefore be cautioned accordingly.

PRECAUTIONS

Confusion, anxiety and tremors have been reported in few patients receiving propoxyphene and orphenadrine concomitantly. As these symptoms may be simply due to an additive effect, reduction of dosage and/or discontinuation of one or both agents is recommended in such cases.

Orphenadrine citrate should be used with caution in patients with tachycardia, cardiac decompensation, coronary insufficiency, cardiac arrhythmias.

Safety of continuous long-term therapy with orphenadrine citrate has not been established. Therefore, if orphenadrine citrate is prescribed for prolonged use, periodic monitoring of blood, urine and liver function values is recommended.

PREGNANCY

Animal reproduction studies have not been conducted with orphenadrine citrate. It is also not known whether orphenadrine citrate can cause fetal harm when administered to a pregnant woman or can affect reproduction capacity. Orphenadrine citrate should be given to a pregnant woman only if clearly needed.

PEDIATRIC USE

Safety and effectiveness in pediatric patients have not been established.

ADVERSE REACTIONS

Adverse reactions of orphenadrine citrate are mainly due to the mild anti-cholinergic action of orphenadrine citrate and are usually associated with higher dosage. Dryness of the mouth is usually the first adverse effect to appear. When the daily dose is increased, possible adverse effects include tachycardia, palpitation, urinary hesitancy or retention, blurred vision, dilatation of pupils, increased ocular tension, weakness, nausea, vomiting, headache, dizziness, constipation, drowsiness, hypersensitivity reactions, pruritus, hallucinations, agitation, tremor, gastric irritation and rarely urticaria and other dermatoses. Infrequently, an elderly patient may experience some degree of mental confusion. These adverse reactions can usually be eliminated by reduction in dosage. Very rare cases of aplastic anemia associated with the use of orphenadrine tablets have been reported. No causal relationship has been established.

To report SUSPECTED ADVERSE REACTIONS, contact Sandoz Inc. at 1-800-525-8747 or FDA at 1-800-FDA-1088 or www.fda.gov/medwatch.

DRUG ABUSE AND DEPENDENCE

Orphenadrine citrate has been chronically abused for its euphoric effects.[1]The mood elevating effects may occur at therapeutic doses of orphenadrine.[2]

OVERDOSAGE

Orphenadrine citrate is toxic when overdosed and typically induces anticholinergic effects.[3]In a review of orphenadrine toxicity, the minimum lethal dose was found to be 2 to 3 grams for adults; however, the range of toxicity is variable and unpredictable.[4]Treatment for orphenadrine citrate overdose is evacuation of stomach contents (when necessary), charcoal at repeated doses, intensive monitoring and appropriate supportive treatment of any emergent anticholinergic effects.[5]

DOSAGE AND ADMINISTRATION

Adults-Two tablets per day; one in the morning and one in the evening.

HOW SUPPLIED

Orphenadrine Citrate Extended-Release Tablets, USP, for oral administration, are available as

100 mg

White, round-shaped tablets debossed “ E” over “22” on one side and plain on the other side and supplied as:

NDC 0185-0022-01 bottles of 100

NDC 0185-0022-10 bottles of 1000

Store at 20° to 25°C (68° to 77°F) [see USP Controlled Room Temperature].

Dispense contents in a tight, light-resistant container as defined in the USP with a child-resistant closure, as required.

KEEP TIGHTLY CLOSED.

KEEP OUT OF THE REACH OF CHILDREN.

Manufactured by

Sandoz Inc.

Princeton, NJ 08540

46299664

Rev. May 2022

MF0022REV05/2022

Orphenadrine Citrate Extended-Release Tablets, USP, 100 mg x 100 Tablets - Label

NDC 0185-0022-01

Orphenadrine Citrate Extended-Release Tablets, USP

100 mg

Rx only

100 Tablets

Sandoz